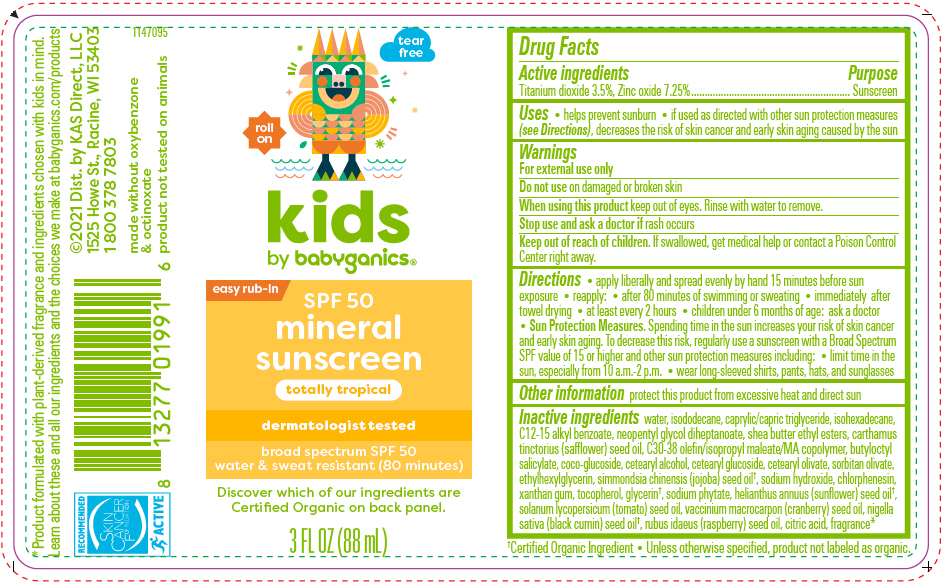 DRUG LABEL: Kids SPF50Plus Mineral Sunscreen Rollerball Totally Tropical
NDC: 59062-2300 | Form: SPRAY
Manufacturer: KAS Direct LLC dba BabyGanics
Category: otc | Type: HUMAN OTC DRUG LABEL
Date: 20241223

ACTIVE INGREDIENTS: Zinc Oxide 7.25 g/100 mL; Titanium Dioxide 3.5 g/100 mL
INACTIVE INGREDIENTS: Water; Isododecane; MEDIUM-CHAIN TRIGLYCERIDES; Isohexadecane; ALKYL (C12-15) BENZOATE; Neopentyl Glycol Diheptanoate; Shea Butter Ethyl Esters; SAFFLOWER OIL; DIDECYLDIMONIUM CHLORIDE; Butyloctyl Salicylate; COCO-GLUCOSIDE; CETOSTEARYL ALCOHOL; Cetearyl Glucoside; Cetearyl Olivate; Sorbitan Olivate; Ethylhexylglycerin; JOJOBA OIL; Sodium Hydroxide; Chlorphenesin; Xanthan Gum; Tocopherol; Glycerin; PHYTATE SODIUM; SUNFLOWER SEED; TOMATO SEED OIL; CRANBERRY SEED; NIGELLA SATIVA SEED OIL; RUBUS IDAEUS SEED; CITRIC ACID MONOHYDRATE

Kids SPF50+ Mineral Sunscreen Rollerball Totally Tropical

Drug Facts

Active ingredients

Titanium dioxide 3.5%, Zinc oxide 7.25%

Purpose

Sunscreen

Uses

- helps prevent sunburn
- if used as directed with other sun protection measures (see Directions), decreases the risk of skin cancer and early skin aging caused by the sun

Warnings

For external use only

Do not use on damaged or broken skin

When using this product keep out of eyes. Rinse with water to remove.

Stop use and ask a doctor if rash occurs

Keep out of reach of children. If swallowed, get medical help or contact a Poison Control Center right away.

Directions

- apply liberally and spread evenly by hand 15 minutes before sun exposure
- reapply:
  - after 80 minutes of swimming or sweating
  - immediately after towel drying
  - at least every 2 hours
- children under 6 months of age: ask a doctor
- Sun Protection Measures. Spending time in the sun increases your risk of skin cancer and early skin aging. To decrease this risk, regularly use a sunscreen with a Broad Spectrum SPF value of 15 or higher and other sun protection measures including:
  - limit time in the sun, especially from 10 a.m.-2 p.m.
  - wear long-sleeved shirts, pants, hats, and sunglasses

Other information

protect this product from excessive heat and direct sun

Inactive ingredients

water, isododecane, caprylic/capric triglyceride, isohexadecane, C12-15 alkyl benzoate, neopentyl glycol diheptanoate, shea butter ethyl esters, carthamus tinctorius (safflower) seed oil, C30-38 olefin/isopropyl maleate/MA copolymer, butyloctyl salicylate, coco-glucoside, cetearyl alcohol, cetearyl glucoside, cetearyl olivate, sorbitan olivate, ethylhexylglycerin, simmondsia chinensis (jojoba) seed oil [Certified Organic Ingredient • Unless otherwise specified, product not labeled as organic.] , sodium hydroxide, chlorphenesin, xanthan gum, tocopherol, glycerin, sodium phytate, helianthus annuus (sunflower) seed oil, solanum lycopersicum (tomato) seed oil, vaccinium macrocarpon (cranberry) seed oil, nigella sativa (black cumin) seed oil, rubus idaeus (raspberry) seed oil, citric acid, fragrance [Product formulated with plant-derived fragrance and ingredients chosen with kids in mind. Learn about these and all our ingredients and the choices we make at babyganics.com/products]

Dist. by KAS Direct, LLC
1525 Howe St., Racine, WI 53403

PRINCIPAL DISPLAY PANEL - 88 mL Bottle Label

tear
free

roll
on

kids
by babyganics®

easy rub-in

SPF 50
mineral
sunscreen

totally tropical

dermatologist tested

broad spectrum SPF 50
water & sweat resistant (80 minutes)

Discover which of our ingredients are
Certified Organic on back panel.

3 FL OZ (88 mL)